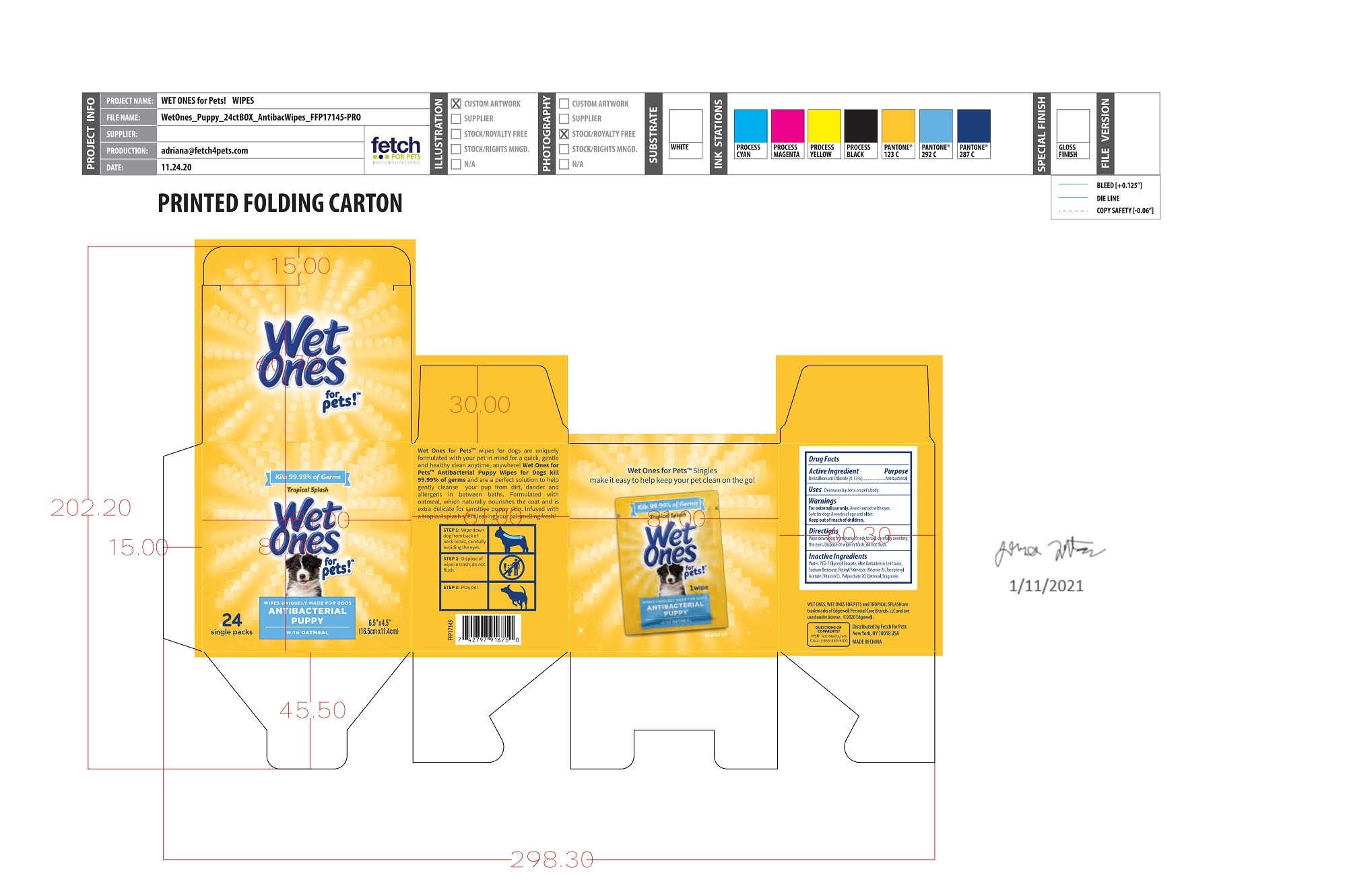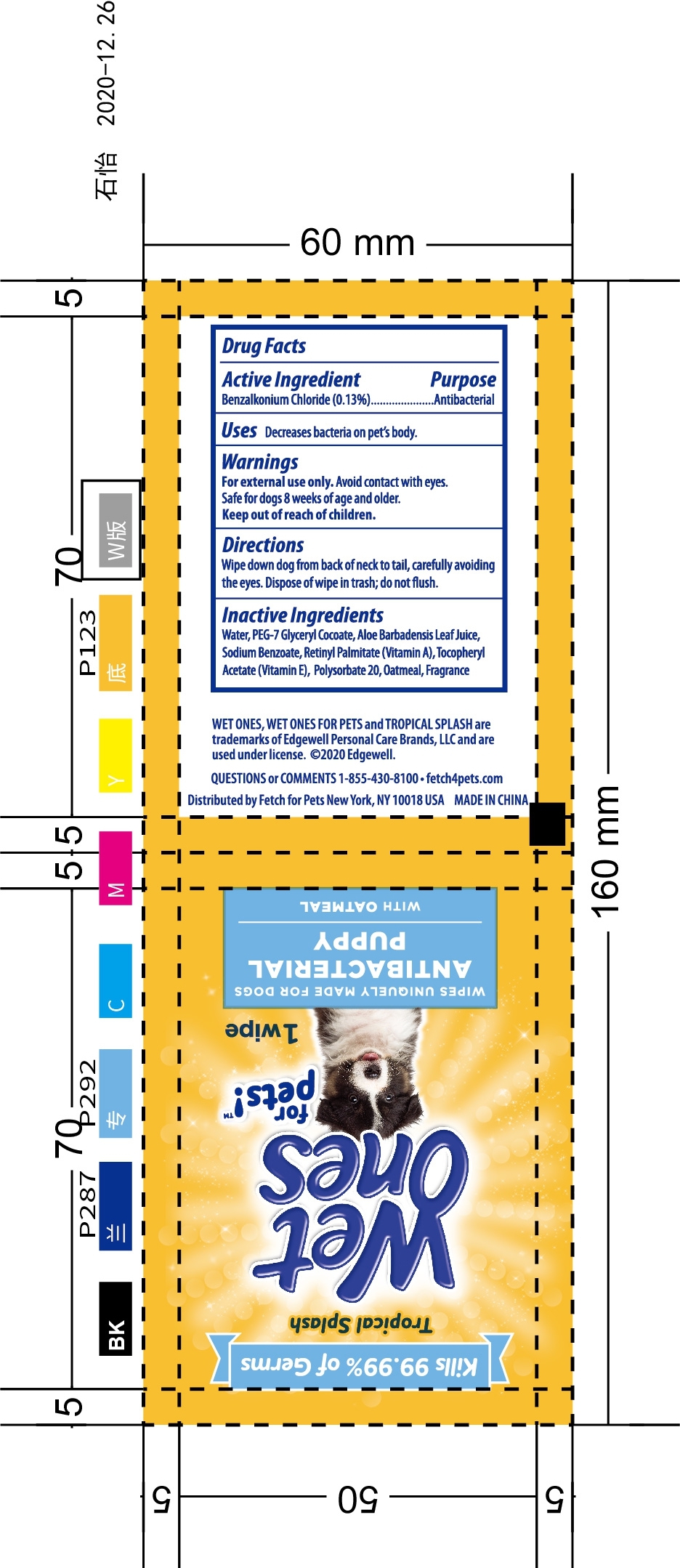 DRUG LABEL: ANTIBACTERIAL PUPPY WIPES
NDC: 77720-023 | Form: CLOTH
Manufacturer: Skaffles Group Limited Liability Company
Category: animal | Type: OTC ANIMAL DRUG LABEL
Date: 20210119

ACTIVE INGREDIENTS: BENZALKONIUM CHLORIDE 0.13 g/100 g
INACTIVE INGREDIENTS: WATER; VITAMIN A PALMITATE; .ALPHA.-TOCOPHEROL ACETATE; ALOE VERA LEAF; POLYSORBATE 20; OATMEAL; SODIUM BENZOATE; PEG-7 GLYCERYL COCOATE

Active Ingredient

Benzalkonium Chloride 0.13%

Purpose

Antibacterial

USE

Decreases Bacteria on pets body.

Warning

For external use only.

Avoid Contact with eyes. Safe for dogs 8 weeks of age and older.

Keep out of reach of children.

Directions

Wipe down dog from back of neck to tail,carefully avoiding the eyes.

didpose of wipe in trash ,do not flush

Inactive ingredients

Water, PEG-7 GlycerylCocoate,Aloe Barbadensis Leaf Juice,Sodium Benzoate,Retinyl Palmitate (Vitamin A),TocopherylAcetate(Vitamin E), Polysorbate 20,0atmeal, Fragrance.